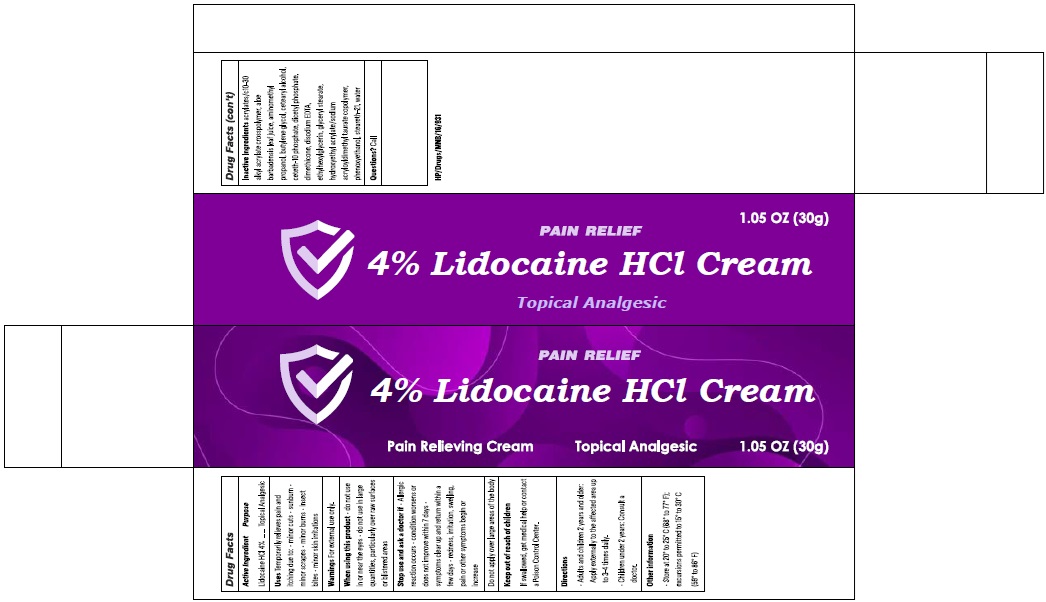 DRUG LABEL: LidoGuard
NDC: 73492-272 | Form: CREAM
Manufacturer: ALAINA HEALTHCARE PRIVATE LIMITED
Category: otc | Type: HUMAN OTC DRUG LABEL
Date: 20251209

ACTIVE INGREDIENTS: LIDOCAINE HYDROCHLORIDE 4 g/100 g
INACTIVE INGREDIENTS: ACRYLATES/C10-30 ALKYL ACRYLATE CROSSPOLYMER (60000 MPA.S); ALOE VERA LEAF JUICE; AMINOMETHYLPROPANOL; BUTYLENE GLYCOL; CETOSTEARYL ALCOHOL; CETETH-10 PHOSPHATE; DIHEXADECYL PHOSPHATE; DIMETHICONE, UNSPECIFIED; EDETATE DISODIUM; ETHYLHEXYLGLYCERIN; GLYCERYL MONOSTEARATE; HYDROXYETHYL ACRYLATE/SODIUM ACRYLOYLDIMETHYL TAURATE COPOLYMER (100000 MPA.S AT 1.5%); PHENOXYETHANOL; STEARETH-21; WATER

4% Lidocaine HCl Cream

Active Ingredient Purpose

Lidocaine HCl 4%.............................................Topical Analgesic

Uses

Temporarily relieves pain and itching due to:

- minor cuts
- sunburn
- minor scrapes
- minor burns
- insect bites
- minor skin irritations

Warnings

For external use only.

When using this product

- do not use in or near the eyes
- do not use in large quantities, particularly over raw surfaces or blistered areas

Stop use and ask a doctor if

- Allergic reaction occurs
- condition worsens or does not improve within 7 days
- symptoms clear up and return within a few days
- redness, irritation, swelling, pain or other symptoms begin or increase

DO NOT USE

Do not apply over large areas of the body

Keep out of reach of children

If swallowed, get medical help or contact a Poison Control Center.

Directions

- Adults and children 2 years and older: Apply externally to the affected area up to 3-4 times daily.
- Children under 2 years: Consult a doctor.

Other information

- Store at 20° to 25° C (68° to 77° F); excursions permitted to 15° to 30° C (59° to 86° F)

lnactive lngredients

acrylates/cl0-30 alkyl acrylate crosspolymer, aloe barbadensis leaf juice, aminomethyl propanol, butylene glycol, cetearyl alcohol, ceteth-10 phosphate, dicetyl phosphate, dimethicone, disodium EDTA, ethylhexylglycerin, glyceryl stearate, hydroxyethyl acrylate/sodium acryloyldimethyl taurate copolymer, phenoxyethanol, steareth-21, water

Questions?

Call

PRINCIPAL DISPLAY PANEL

Pain Relief
4% Lidocaaine HCl Cream
Pain Relieving Cream
Topical Analgesic
1.05 oz (30g)